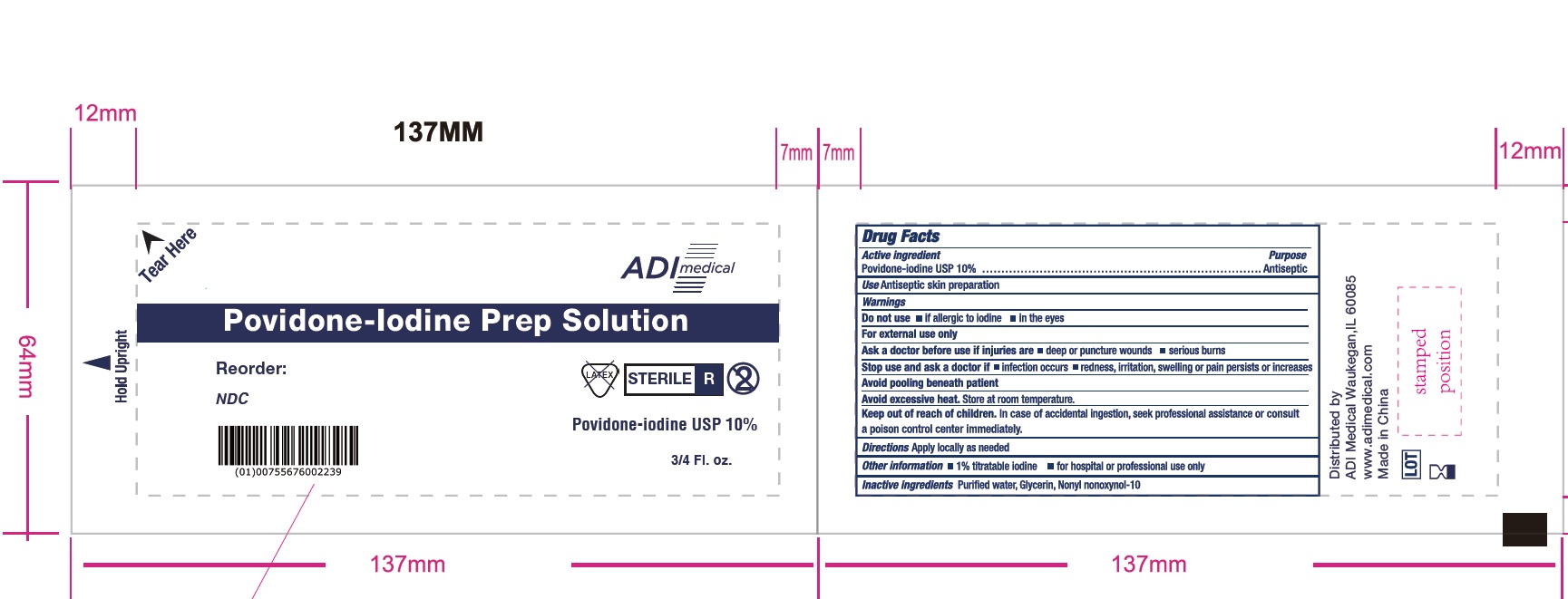 DRUG LABEL: sterile
NDC: 83645-552 | Form: SOLUTION
Manufacturer: Asia Dynamics Inc., d/b/a ADI Medical
Category: otc | Type: HUMAN OTC DRUG LABEL
Date: 20250108

ACTIVE INGREDIENTS: POVIDONE-IODINE 10 g/100 g
INACTIVE INGREDIENTS: NONOXYNOL-10; GLYCERIN; WATER

Povidone-Iodine Solution, sterile

Active ingredient

Povidone-lodine USP 10%

Purpose

Antiseptic

Use

for antiseptic skin preparation

Warnings

For external use only

Avoid pooling beneath patient

do not use

- if allergic to lodine
- in the eye

Stop use and ask a doctor if

- redness, irritation, swelling or pain persists or increases
- infection occurs

Keep out of reach of children.

In case of accidental ingestion, seek professional assistance or consult a poison control center immediately.

Ask a doctor before use if injuries are

- deep or puncture wounds
- serious burns

Directions

apply locally as needed

Other information

- 1% titratable iodine
- for hospital or professional use only

Inactive ingredients:

Nonyl Nonoxynol-10, Glycerin, Purifed Water.

Storage

Avoid excessive heat

Store at room temperature

Package Labeling:

NDC 83645-552-11

ADI Medical